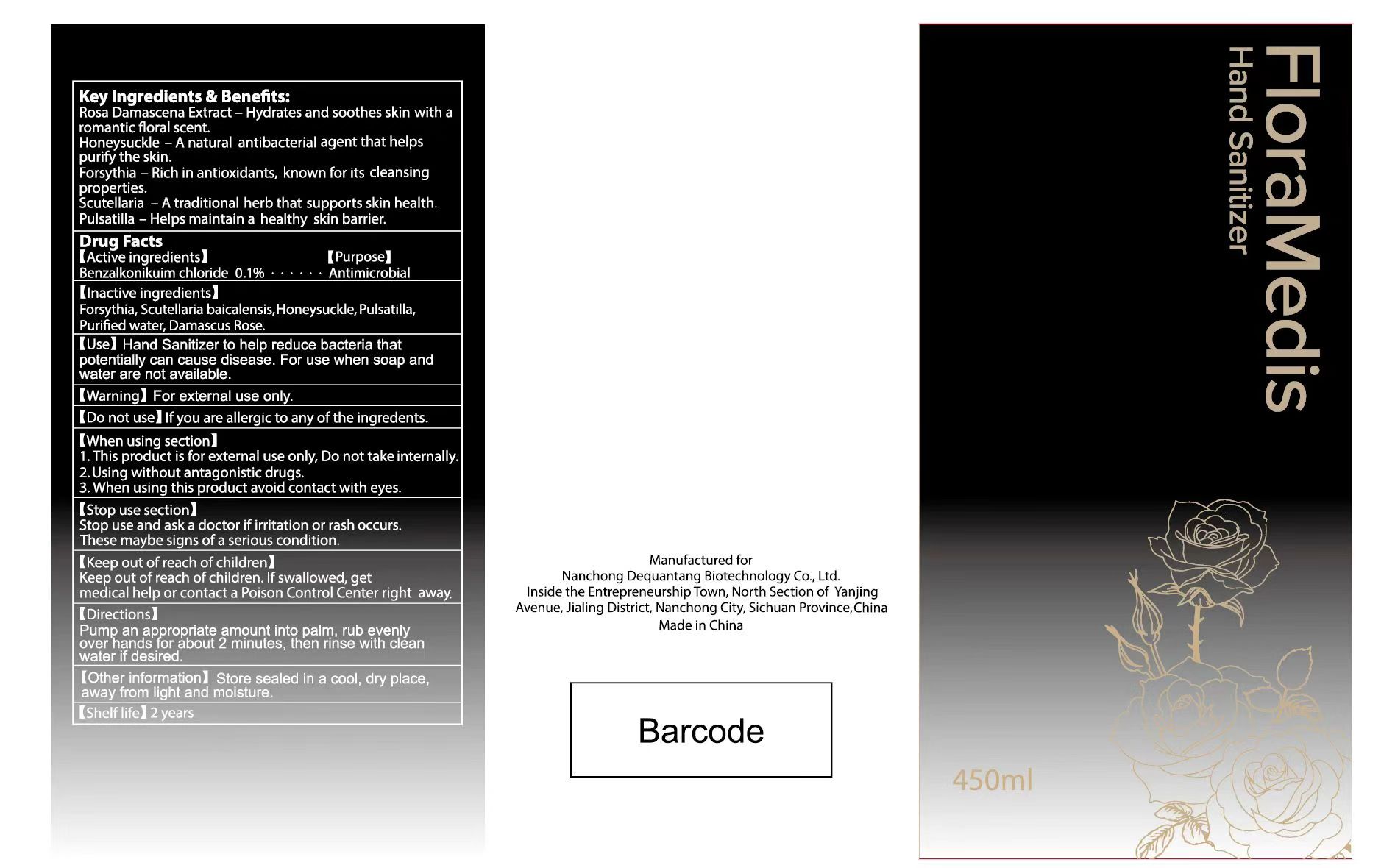 DRUG LABEL: FloraMedis Hand Sanitizer
NDC: 87215-001 | Form: LIQUID
Manufacturer: Sichuan Pengtai Qifan Technology Co., Ltd
Category: otc | Type: HUMAN OTC DRUG LABEL
Date: 20251121

ACTIVE INGREDIENTS: BENZALKONIUM CHLORIDE 0.1 g/100 mL
INACTIVE INGREDIENTS: SCUTELLARIA BAICALENSIS WHOLE; SIMIARENOL; ANEMONIN; WATER; PHILLYRIN; ROSE OIL

87215-001

Active Ingredient

Benzalkonium chloride 0.1%

Purpose

Antimicrobial

Use

Hand Santizer to help reduce bacteria that potentially can cause disease. For use when soap and water are not available.

Warnings

For external use only.

Do not use

If you are allergic to any of the ingredents.

When Using

1.This product is for external use only, Do not take internally.
2.Using without antagonistic drugs.
3.When using this product avoid contact with eyes.

Stop Use

Stop use and ask a doctor if irritation or rash occurs.
These maybe signs of a serious condition.

Keep out of reach of children.lfswallowed, get
medical help or contact a Poison Control Center right away.

Directions

Pump an appropriate amount into palm, rub evenly
over hands for about 2 minutes, then rinse with clean water if desired.

Other information

Store sealed in a cool, dry place, away from light and moisture.

Shelf life: 2 years

INACTIVE

Forsythia, Scutellaria baicalensis, honeysuckle, Pulsatilla, Purified water, Damascus Rose